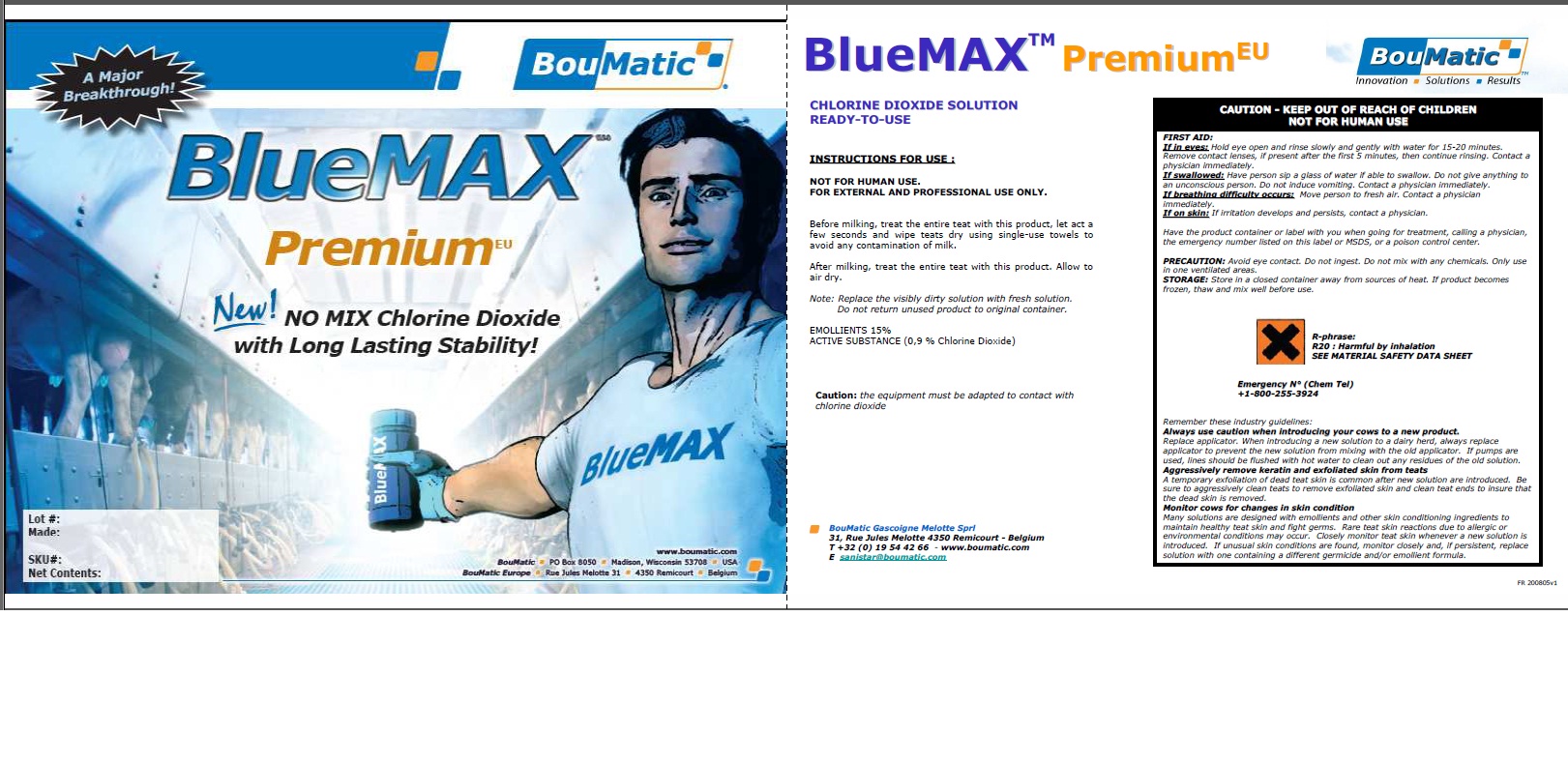 DRUG LABEL: BlueMAX Premium EU
NDC: 48106-1195 | Form: LIQUID
Manufacturer: BouMatic, LLC
Category: animal | Type: OTC ANIMAL DRUG LABEL
Date: 20130101

ACTIVE INGREDIENTS: CHLORINE DIOXIDE 32 g/10 L

BLUEMAX PREMIUM EU

INDICATIONS AND USAGE

CHLORINE DIOXIDE SOLUTION
READY-TO-USE
INSTRUCTIONS FOR USE :
NOT FOR HUMAN USE.
FOR EXTERNAL AND PROFESSIONAL USE ONLY.
Before milking, treat the entire teat with this product, let act a
few seconds and wipe teats dry using single-use towels to
avoid any contamination of milk.
After milking, treat the entire teat with this product. Allow to
air dry.
Note: Replace the visibly dirty solution with fresh solution.
Do not return unused product to original container.
EMOLLIENTS 15%
ACTIVE SUBSTANCE (0,9 % Chlorine Dioxide)
Caution: the equipment must be adapted to contact with
chlorine dioxide

PEDIATRIC USE

FIRST AID:
If in eyes: Hold eye open and rinse slowly and gently with water for 15-20 minutes.
Remove contact lenses, if present after the first 5 minutes, then continue rinsing. Contact a
physician immediately.
If swallowed: Have person sip a glass of water if able to swallow. Do not give anything to
an unconscious person. Do not induce vomiting. Contact a physician immediately.
If breathing difficulty occurs: Move person to fresh air. Contact a physician
immediately.
If on skin: If irritation develops and persists, contact a physician.
Have the product container or label with you when going for treatment, calling a physician,
the emergency number listed on this label or MSDS, or a poison control center.
PRECAUTION: Avoid eye contact. Do not ingest. Do not mix with any chemicals. Only use
in one ventilated areas.
STORAGE: Store in a closed container away from sources of heat. If product becomes
frozen, thaw and mix well before use.
Remember these industry guidelines:
Always use caution when introducing your cows to a new product.
Replace applicator. When introducing a new solution to a dairy herd, always replace
applicator to prevent the new solution from mixing with the old applicator. If pumps are
used, lines should be flushed with hot water to clean out any residues of the old solution.
Aggressively remove keratin and exfoliated skin from teats
A temporary exfoliation of dead teat skin is common after new solution are introduced. Be
sure to aggressively clean teats to remove exfoliated skin and clean teat ends to insure that
the dead skin is removed.
Monitor cows for changes in skin condition
Many solutions are designed with emollients and other skin conditioning ingredients to
maintain healthy teat skin and fight germs. Rare teat skin reactions due to allergic or
environmental conditions may occur. Closely monitor teat skin whenever a new solution is
introduced. If unusual skin conditions are found, monitor closely and, if persistent, replace
solution with one containing a different germicide and/or emollient formula